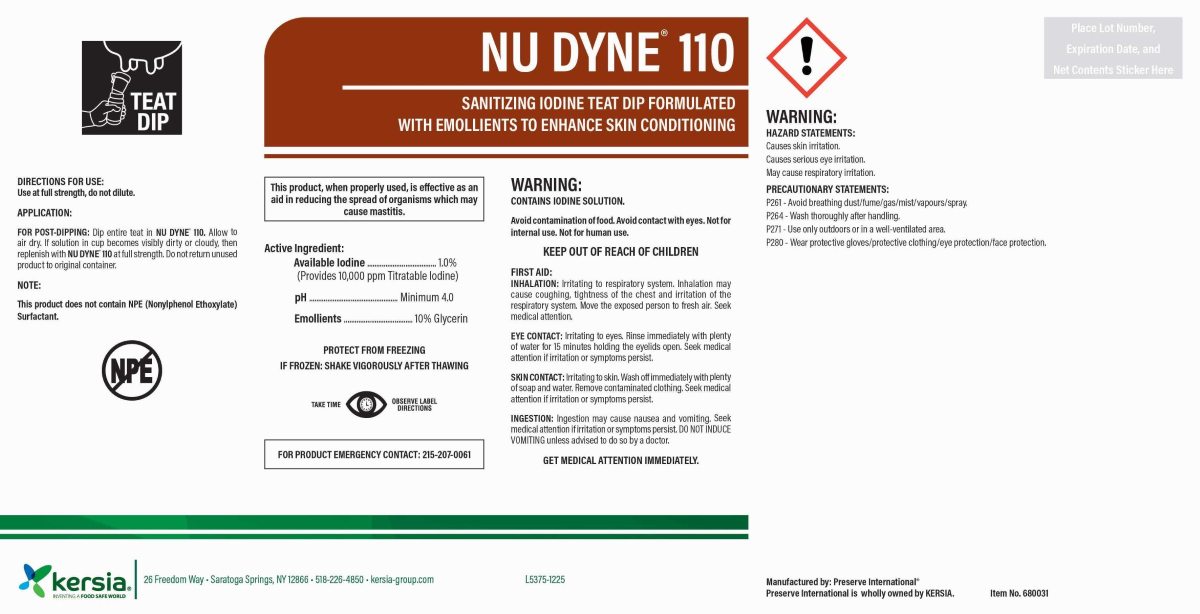 DRUG LABEL: NU DYNE 110
NDC: 60648-9000 | Form: SOLUTION
Manufacturer: Preserve Inc.
Category: animal | Type: OTC ANIMAL DRUG LABEL
Date: 20251230

ACTIVE INGREDIENTS: IODINE 10.22 g/1 L; GLYCERIN 103.02 g/1 L

NU-Dyne® 110

USE DIRECTIONS:

Use at full strength, do not dilute.

APPLICATION:

For post-dipping: Dip Entire teat in NU DYNE® 110. Allow
to air dry. If solution in cup becomes visibly
dirty or cloudy, then replenish with NU-DYNE® 110
at full strength. Do not return unused product
to original container.

NOTE:

This product does not contain NPE (Nonylphenol Ethoxylate) Surfactant.

WARNINGS AND PRECAUTIONS

PROTECT FROM FREEZING

IF FROZEN: SHAKE VIGOROUSLY AFTER THAWING

WARNINGS AND PRECAUTIONS

TAKE TIME OBSERVE LABEL DIRECTIONS

WARNING:

CONTAINS IODINE SOLUTION.

Avoid contamination of food. Avoid contact with eyes. Not for internal use. Not for human use.

KEEP OUT OF REACH OF CHILDREN

FIRST AID:

INHALATION: Irritating to respiratory system. Inhalation may cause coughing, tightness of the chest and irritation of the respiratory system. Move the exposed person to fresh air. Seek medical attention.

EYECONTACT: Irritating to the eyes. Rinse immediately with plenty of water for 15 minutes holding te eyelids open. Seek medical attention if irritation or symptoms persist.

SKIN CONTACT: Irritating to skin. Wash off immediately with plenty of soap and water. Remove contaminated clothing. Seek medical attention if irritation or symptoms persist.

INGESTION: Ingestion may cause nausea and vomiting. Seek medical attention if irritation or symptoms persist. DO NOT INDUCE VOMITING unless advised to do so by a doctor.
GET MEDICAL ATTENTION IMMEDIATELY.

FOR PRODUCT EMERGENCY CONTACT: 215-207-0061

HAZARD STATEMENTS:

Causes skin irritation.

Causes serious eye irritation.

May cause respiratory irritation.

PRECAUSTIONARY STATEMENTS:

P261 - Avoid breathing dust/fume/gas/mist/vapours/spray.

P264 - Wash thoroughly after handling.

P271 - Use only outdoors or in a well-ventilated area.

P280 - Wear protective gloves/protective clothing/eye protection/face protection.

PACKAGE LABEL

NU-DYNE® 110

SANITIZING IODINE TEAT DIP FORMULATED WITH
EMOLLIENTS TO ENHANCE SKIN CONDITIONING

This product, when properly used, is effective as an aid
in reducing the spread of organisms which may cause
mastitis.

Active Ingredient..........1.00% Available Iodine (provides 10,000 ppm titratable iodine)
pH.....................................Minimum 4.0
Emollients........................10% Glycerin

Manufactured By: Preserve International®

Preserve International® is wholly owned by KERSIA.

Kersia®

26 Freedom Way

Saratoga Springs, NY 12866

518-226-4850

Kersia-group.com